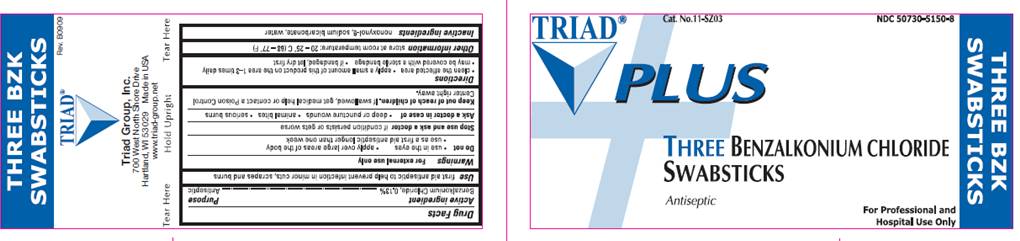 DRUG LABEL: BZK Plus Swabsticks
NDC: 50730-5150 | Form: SOLUTION
Manufacturer: H and P Industries, Inc. dba Triad Group
Category: otc | Type: HUMAN OTC DRUG LABEL
Date: 20091229

ACTIVE INGREDIENTS: benzalkonium chloride 0.0013 mL/1 mL
INACTIVE INGREDIENTS: nonoxynol-9; sodium bicarbonate; water

DRUG FACTS

ACTIVE INGREDIENT

Benzalkonium chloride .13%

PURPOSE

Antiseptic

USE

First Aid Antiseptic to help prevent the risk of infection in minor cuts, scrapes and burns

WARNINGS

For external use only.

Do not

- use in the eyes
- apply over large areas of the body
- use as a first aid antiseptic for longer than 1 week unless directed by a doctor

Ask a doctor in case of

- deep or puncture wounds
- animal bites
- serious burns

Stop use and ask a doctor

if condition persists or gets worse

Keep out of reach of children

If swallowed, get medical help or contact a Poison Control Center right away.

DIRECTIONS

- clean the affected area

- apply a small amount of this product to the area 1-3 times daily
- may be covered with a sterile bandage
- if bandaged, let dry first

OTHER INFORMATION

Store at room temperature 20° - 25° C (68° - 77° F)

INACTIVE INGREDIENTS

nonoxynol-9, sodium bicarbonate, water

POUCH INFORMATION

TRIAD PLUS
Cat. No. 11-SZ03
NDC 50730-5150-8
THREE BENZALKONIUM CHLORIDE
SWABSTICKS
Antiseptic
For Professional and Hospital Use Only
Triad Group, Inc.
700 West North Shore Drive
Hartland, WI 53029 Made in USA
www.triad-group.net